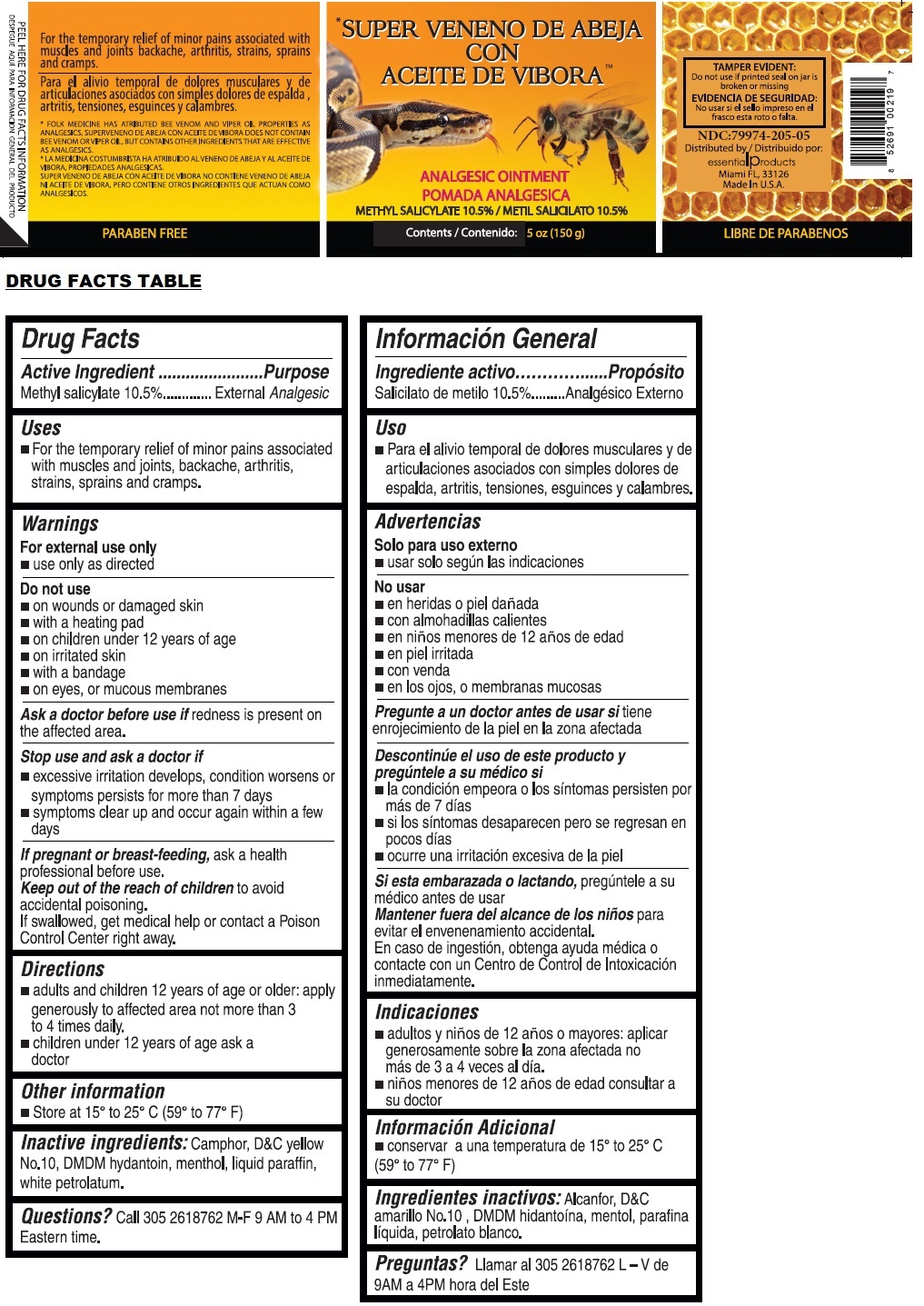 DRUG LABEL: Veneno de Abeja
                                    
NDC: 79974-205 | Form: OINTMENT
Manufacturer: Miramar Cosmetics, Inc DBA Miramar Lab
Category: otc | Type: HUMAN OTC DRUG LABEL
Date: 20241223

ACTIVE INGREDIENTS: METHYL SALICYLATE 15.75 g/150 g
INACTIVE INGREDIENTS: CAMPHOR (NATURAL); D&C YELLOW NO. 10; DMDM HYDANTOIN; MENTHOL, UNSPECIFIED FORM; PARAFFIN; PETROLATUM

SUPER VENENO DE ABEJA CON ACEITE DE VIBORA

Active Ingredient

Methyl salicylate 10.5%

Purpose

External Analgesic

Uses

• For the temporary relief of minor pains associated with muscles and joints, backache, arthritis, strains, sprains, and cramps.

Warnings

For external use only
• use only as directed

Do not use
• on wounds or damaged skin
• with a heating pad
• on children under 12 years of age
• on irritated skin
• with a bandage
• on eyes, or mucous membranes

Ask a doctor before use if redness is present on the affected area.

Stop use and ask a doctor if
• excessive irritation develops, condition worsens or symptoms persists for more than 7 days
• symptoms clear up and occur again within a few days

If pregnant or breast-feeding, ask a heath professional before use.

Keep out of reach of children to avoid accidental poisoning.
If swallowed, get medical help or contact a Poison Control Center right away.

Directions

• adults and children 12 years of age or older: apply generously to affected area not more than 3 to 4 times daily.
• children under 12 years of age ask a doctor

Other Information

• Store at 15° to 25° C (59° to 77° F)

Inactive ingredients:

Camphor, D&C yellow No.10, DMDM hydantoin, menthol, liquid paraffin, white petrolatum.

Questions?

Call 305 2618762 M-F 9AM to 4PM Eastern time.

TAMPER EVIDENT:
Do not use if printed seal on jar is broken or missing

Distributed by
essentialproducts
Miami, FL, 33126
Made In U.S.A.

PARABEN FREE